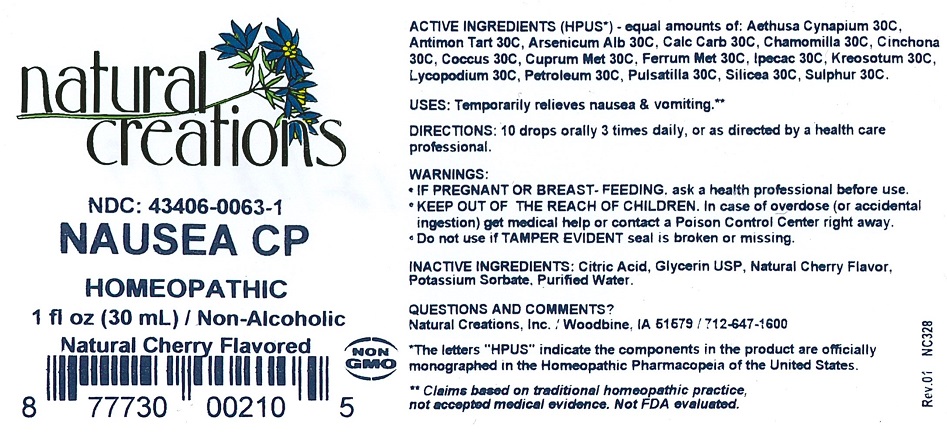 DRUG LABEL: Nausea CP
NDC: 43406-0063 | Form: LIQUID
Manufacturer: Natural Creations, Inc
Category: homeopathic | Type: HUMAN OTC DRUG LABEL
Date: 20181221

ACTIVE INGREDIENTS: AETHUSA CYNAPIUM WHOLE 30 [hp_C]/1 mL; ANTIMONY POTASSIUM TARTRATE 30 [hp_C]/1 mL; ARSENIC TRIOXIDE 30 [hp_C]/1 mL; OYSTER SHELL CALCIUM CARBONATE, CRUDE 30 [hp_C]/1 mL; MATRICARIA CHAMOMILLA WHOLE 30 [hp_C]/1 mL; CINCHONA OFFICINALIS BARK 30 [hp_C]/1 mL; PROTORTONIA CACTI 30 [hp_C]/1 mL; COPPER 30 [hp_C]/1 mL; IRON 30 [hp_C]/1 mL; IPECAC 30 [hp_C]/1 mL; WOOD CREOSOTE 30 [hp_C]/1 mL; LYCOPODIUM CLAVATUM SPORE 30 [hp_C]/1 mL; KEROSENE 30 [hp_C]/1 mL; PULSATILLA VULGARIS WHOLE 30 [hp_C]/1 mL; SILICON DIOXIDE 30 [hp_C]/1 mL; SULFUR 30 [hp_C]/1 mL
INACTIVE INGREDIENTS: CITRIC ACID MONOHYDRATE; GLYCERIN; POTASSIUM SORBATE; WATER

Nausea CP

ACTIVE INGREDIENT

ACTIVE INGREDIENTS (*HPUS) - equal amounts of: Aethusa Cynapium 30C, Antimon Tart 30C, Arsenicum Alb 30C, Calc Carb 30C, Chamomilla 30C, Cinchona 30C, Coccus 30C, Cuprum Met 30C, Ferrum Met 30C, Ipecac 30C, Kreosotum 30C, Lycopodium 30C, Petroleum 30C, Pulsatilla 30C, Silicea 30C, Sulphur 30C

INDICATIONS AND USAGE

USES: Temporarily relieves nausea & vomiting.**

PURPOSE

USES: Temporarily relieves nausea & vomiting.**

DOSAGE AND ADMINISTRATION

DIRECTIONS: 10 drops orally 3 times daily, or as directed by a health care professional.

KEEP OUT OF REACH OF CHILDREN

KEEP OUT OF THE REACH OF CHILDREN. In case of overdose (or accidental ingestion) get medical help or contact a Poison Control Center right away.

WARNINGS:

- IF PREGNANT OR BREAST-FEEDING, ask a health care professional before use.
- KEEP OUT OF THE REACH OF CHILDREN. In case of overdose (or accidental ingestion) get medical help or contact a Poison Control Center right away.
- Do not use if TAMPER EVIDENT seal is broken or missing.

INACTIVE INGREDIENT

INACTIVE INGREDIENTS: Citric Acid, Glycerin USP, Natural Cherry Flavor, Potassium Sorbate, Purified Water

QUESTIONS & COMMENTS?

Natural Creations, Inc. / Woodbine, IA 51579 / 712-647-1600

REFERENCES

*The letters "HPUS" indicate the components in the product are officially monographed in the Homeopathic Pharmacopeia of the United States.

**Claims based on traditional homeopathic practice, not accepted medical evidence. Not FDA evaluated.

PACKAGE LABEL

NDC:43406-0063-1

Nausea CP

HOMEOPATHIC

1 fl oz (30mL) / Non-Alcoholic